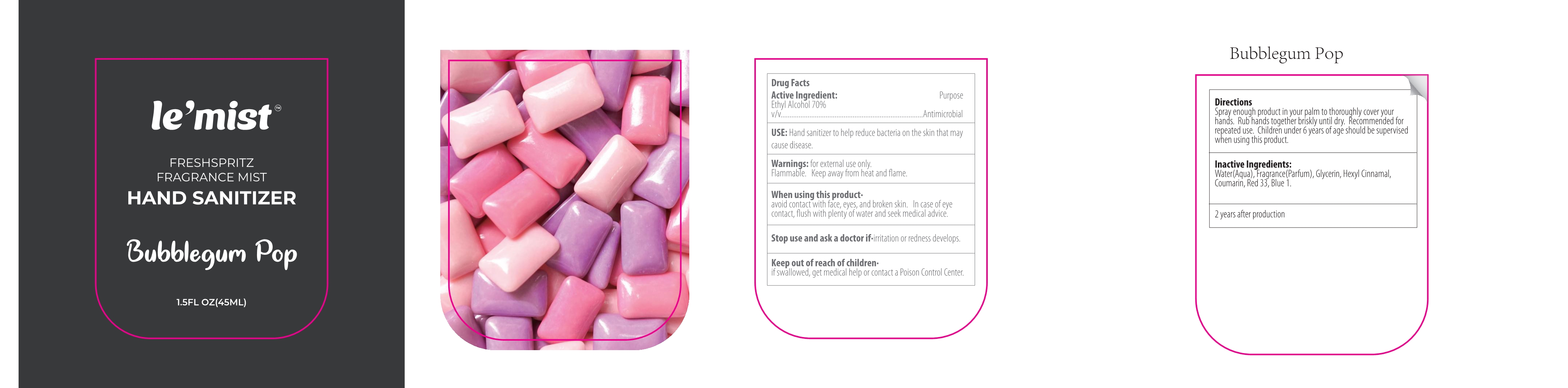 DRUG LABEL: Bubblegum Pop Hand Sanitizer
NDC: 41366-080 | Form: LIQUID
Manufacturer: Zhejiang Meimi Technology Co., Ltd.
Category: otc | Type: HUMAN OTC DRUG LABEL
Date: 20250610

ACTIVE INGREDIENTS: ALCOHOL 70 mL/100 mL
INACTIVE INGREDIENTS: GLYCERIN; WATER; COUMARIN; .ALPHA.-HEXYLCINNAMALDEHYDE; D&C RED NO. 33; FD&C BLUE NO. 1

Zhejiang Meimi Technology Co., Ltd.
Bubblegum Pop Hand Sanitizer 45ml
41366-080-01

Active Ingredient(s)

Ethyl Alcohol 70% v/v

Purpose

Antimicrobial

Use

Hand sanitizer to help reduce bacteria on the skin that may cause disease.

Warnings

- for external use only.
- Flammable.
- Keep away from heat and flame.

Stop use and ask a doctor if·irritation or redness develops.

Keep out of reach of children·
if swallowed, get medical help or contact a Poison Control Center.

Directions

Spray enough product in your palm to thoroughly cover your hands. Rub hands together briskly until dry. Recommended for repeated use. Children under 6 years of age should be supervised when using this product.

Inactive ingredients

Water(Aqua), Fragrance(Parfum), Glycerin, Hexyl Cinnamal, Coumarin, Red 33, Blue 1.

Package Label - Principal Display Panel

45 mL in 1 BOTTLE

NDC: 41366-080-01